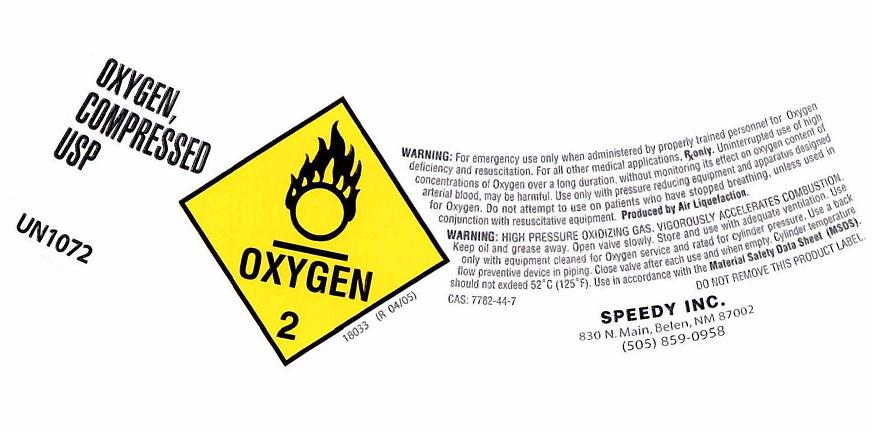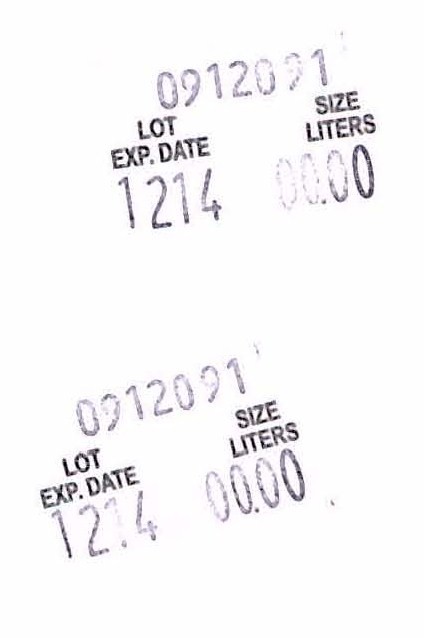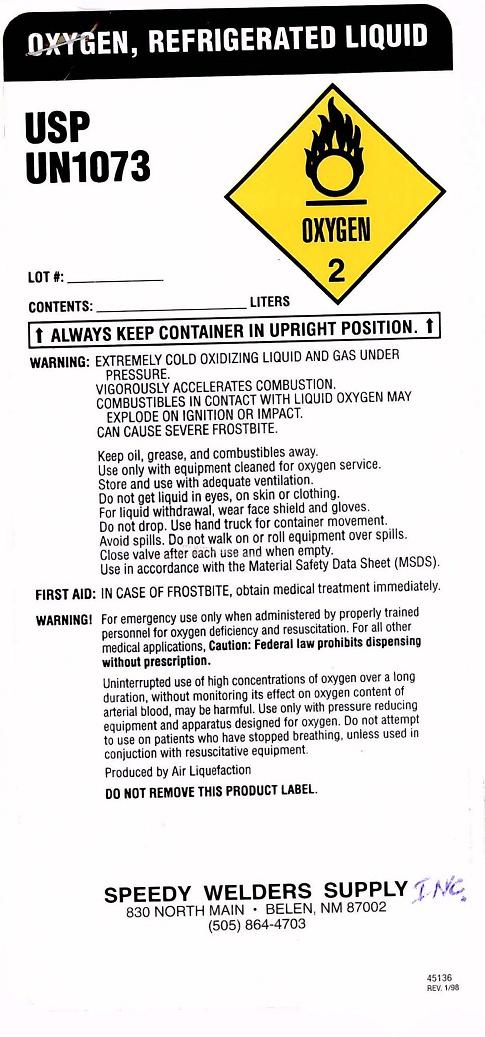 DRUG LABEL: Oxygen
NDC: 54591-001 | Form: GAS
Manufacturer: Speedy Inc.
Category: prescription | Type: HUMAN PRESCRIPTION DRUG LABEL
Date: 20091223

ACTIVE INGREDIENTS: Oxygen 99 L/100 L

Oxygen